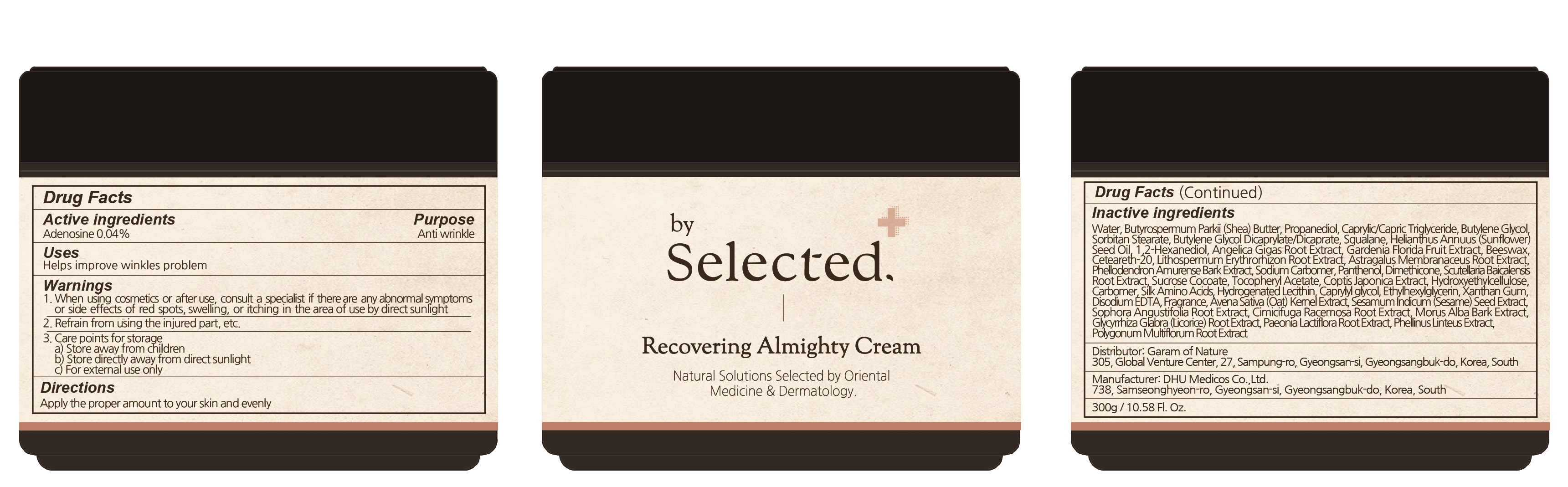 DRUG LABEL: by Selected Recovering Almighty
NDC: 73509-090 | Form: CREAM
Manufacturer: Garam Of Nature
Category: otc | Type: HUMAN OTC DRUG LABEL
Date: 20220428

ACTIVE INGREDIENTS: ADENOSINE 0.04 g/100 g
INACTIVE INGREDIENTS: Water; SHEA BUTTER; Propanediol

ACTIVE INGREDIENT

ADENOSINE 0.04%

INACTIVE INGREDIENT

Water, Butyrospermum Parkii (Shea) Butter, Propanediol, Caprylic/Capric Triglyceride, Butylene Glycol, Sorbitan Stearate, Butylene Glycol Dicaprylate/Dicaprate, Squalane, Helianthus Annuus (Sunflower) Seed Oil, 1,2-Hexanediol, Angelica Gigas Root Extract, Gardenia Florida Fruit Extract, Beeswax, Ceteareth-20, Lithospermum Erythrorhizon Root Extract, Astragalus Membranaceus Root Extract, Phellodendron Amurense Bark Extract, Sodium Carbomer, Panthenol, Dimethicone, Scutellaria Baicalensis Root Extract, Sucrose Cocoate, Tocopheryl Acetate, Coptis Japonica Extract, Hydroxyethylcellulose, Carbomer, Silk Amino Acids, Hydrogenated Lecithin, Caprylyl glycol, Ethylhexylglycerin, Xanthan Gum, Disodium EDTA, Fragrance, Avena Sativa (Oat) Kernel Extract, Sesamum Indicum (Sesame) Seed Extract, Sophora Angustifolia Root Extract, Cimicifuga Racemosa Root Extract, Morus Alba Bark Extract, Glycyrrhiza Glabra (Licorice) Root Extract, Paeonia Lactiflora Root Extract, Phellinus Linteus Extract, Polygonum Multiflorum Root Extract

PURPOSE

Anti-wrinkle

WARNINGS

1. When using cosmetics or after use, consult a specialist if there are any abnormal symptoms or side effects of red spots, swelling, or itching in the area of use by direct sunlight
2. Refrain from using the injured part, etc.
3. Care points for storage and handling
a) Store away from children
b) Store directly away from direct sunlight
c) For external use only

KEEP OUT OF REACH OF CHILDREN

Store away from children

Uses

■ Helps improve wrinkle problem.

Directions

■ Apply an appropriate amount evenly on the skin.

Other Information

■ Do not store this product in an inappropriate place such as high or low temperatures or under direct sun light

Questions

www.byselected.co.kr
byselected@naver.com
+82-70-8883-2525